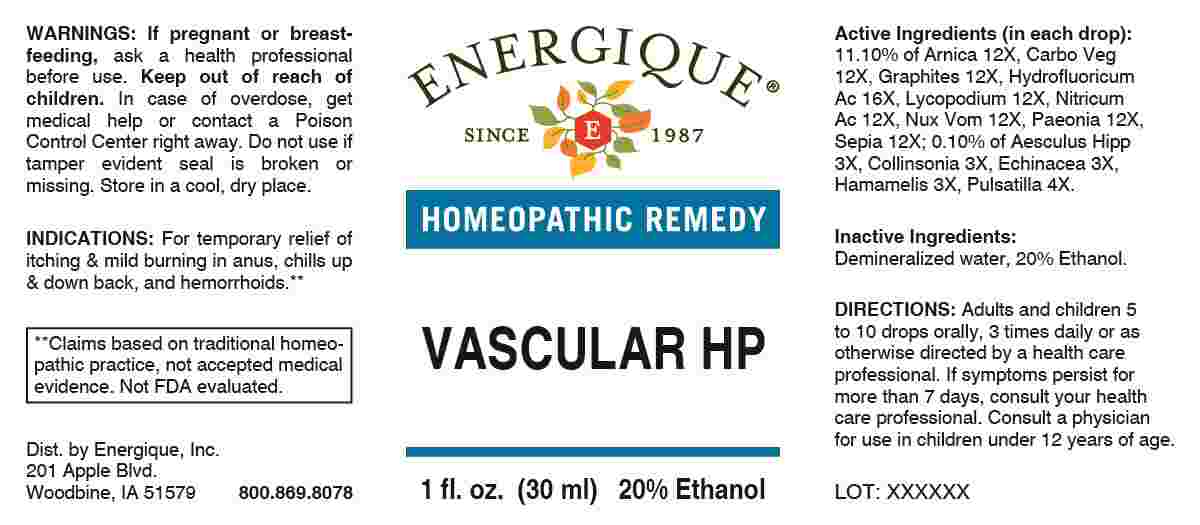 DRUG LABEL: Vascular
NDC: 44911-0727 | Form: LIQUID
Manufacturer: Energique, Inc.
Category: homeopathic | Type: HUMAN OTC DRUG LABEL
Date: 20250129

ACTIVE INGREDIENTS: HORSE CHESTNUT 3 [hp_X]/1 mL; COLLINSONIA CANADENSIS ROOT 3 [hp_X]/1 mL; ECHINACEA ANGUSTIFOLIA WHOLE 3 [hp_X]/1 mL; HAMAMELIS VIRGINIANA ROOT BARK/STEM BARK 3 [hp_X]/1 mL; PULSATILLA PRATENSIS WHOLE 4 [hp_X]/1 mL; ARNICA MONTANA WHOLE 12 [hp_X]/1 mL; ACTIVATED CHARCOAL 12 [hp_X]/1 mL; GRAPHITE 12 [hp_X]/1 mL; LYCOPODIUM CLAVATUM SPORE 12 [hp_X]/1 mL; NITRIC ACID 12 [hp_X]/1 mL; STRYCHNOS NUX-VOMICA SEED 12 [hp_X]/1 mL; PAEONIA OFFICINALIS ROOT 12 [hp_X]/1 mL; SEPIA OFFICINALIS JUICE 12 [hp_X]/1 mL; HYDROFLUORIC ACID 16 [hp_X]/1 mL
INACTIVE INGREDIENTS: WATER; ALCOHOL

DRUG FACTS:

ACTIVE INGREDIENTS:

(in each drop): 11.10% of Arnica Montana 12X, Carbo Vegetabilis 12X, Graphites 12X, Hydrofluoricum Acidum 16X, Lycopodium Clavatum 12X, Nitricum Acidum 12X, Nux Vomica 12X, Paeonia Officinalis 12X, Sepia 12X; 0.10% of Aesculus Hippocastanum 3X, Collinsonia Canadensis 3X, Echinacea 3X, Hamamelis Virginiana 3X, Pulsatilla 4X.

PURPOSE:

For temporary relief of itching & mild burning in anus, chills up & down back, and hemorrhoids.**

**Claims based on traditional homeopathic practice, not accepted medical evidence. Not FDA evaluated.

WARNINGS:

If pregnant or breast-feeding, ask a health professional before use.

Keep out of reach of children. In case of overdose, get medical help or contact a Poison Control Center right away.

Do not use if tamper evident seal is broken or missing.

Store in a cool, dry place.

KEEP OUT OF REACH OF CHILDREN:

In case of overdose, get medical help or contact a Poison Control Center right away.

DIRECTIONS:

Adults and children 5 to 10 drops orally, 3 times daily or as otherwise directed by a health care professional. If symptoms persist for more than 7 days, consult your health care professional. Consult a physician for use in children under 12 years of age.

INDICATIONS:

For temporary relief of itching & mild burning in anus, chills up & down back, and hemorrhoids.**

**Claims based on traditional homeopathic practice, not accepted medical evidence. Not FDA evaluated.

INACTIVE INGREDIENTS:

Demineralized water, 20% Ethanol.

QUESTIONS:

Dist. by Energique, Inc.

201 Apple Blvd.

Woodbine, IA 51579

800.869.8078

PACKAGE DISPLAY LABEL:

ENERGIQUE

SINCE 1987

HOMEOPATHIC REMEDY

VASCULAR HP

1 fl. oz. (30 ml)